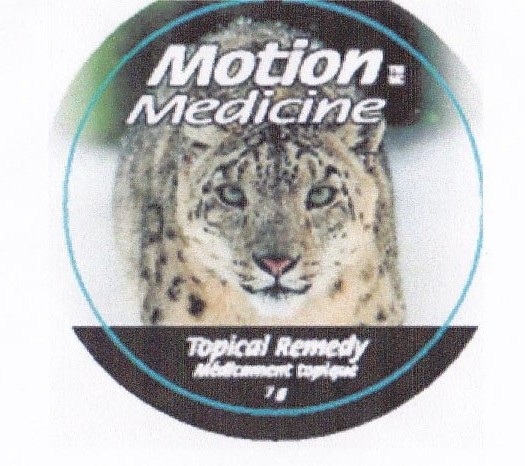 DRUG LABEL: Motion Medicine
								
NDC: 49795-809 | Form: CREAM
Manufacturer: Nutri-Dyn Products Ltd. dba Professional Health Products
Category: otc | Type: HUMAN OTC DRUG LABEL
Date: 20110620

ACTIVE INGREDIENTS: CAMPHOR (NATURAL)     4 g/100 g; Menthol 4 g/100 g
INACTIVE INGREDIENTS: Water; Cetyl alcohol; Glycol stearate; Dimethyl sulfone; Glycerin; Stearyl alcohol; Glucosamine sulfate; C13-14 Isoparaffin; Polysorbate 20; Urea; Phenoxyethanol; Caprylyl glycol; Sorbic acid; Eucalyptus oil; Methyl salicylate; Vitamin E; Lavandula Angustifolia Flower; Thymol; Chondroitin sulfate (bovine); Cucumaria Sea Cucumber; Grape Seed Oil

Motion Medicine

Active Ingredients (Percent by weight) Purpose

Menthol 4.0% ............................Analgesic (Pain reliever)

Camphor 4.0% ...........................Analgesic (Pain reliever)

INDICATIONS AND USAGE

For the temporary relief of minor aches and pains of muscles and joints associated with simple backache, arthritis, strains, bruises and sprains, etc.

Warnings

- Avoid getting into eyes or on mucous membranes.
- If condition worses, or if symptoms persist for more than 7 days or clear up and occur again within a few days, discontinue use of this product and consult a doctor.
- Do not apply to wounds or damaged skin. Do not bandage tightly.

Keep out of the reach of children

- Use only as directed.

- If swallowed, get medical help or contact a Poison Control center right away.

Directions

Adults and children 12 years of age or older: Rub this soothing cream on the affected area not more than 3 to 4 times daily.

Children under the age of 12: Do not use, consult a doctor.

INACTIVE INGREDIENT

C13-14 isoparaffin, caprylyl glycol, cetyl alcohol, chondroitin sulfate, denatured alcohol, eucalyptus oil, glucosamine sulfate, glycerin, grape seed oil, laureth-7, methylsulfonylmethane (MSM), oil of lavender, oil of wintergreen, phenoxyethanol, polyacrylamide, polysorbate-20, sea cucumber extract, sorbic, acid, stearyl alcohol, thymol, urea, vitamin E, water

REFERENCES

Distributed by:

Motion Medicine Inc.

Suite 258, 132-250 Shawville Blvd. SE

Calgary, AB CANADA T2Y 2Z7

1-866-972-8466

120g

PURPOSE

Pain Reliever

PACKAGE LABEL

Motion Medicine

Eases pain, improves movement, and is highly effective

Topical Remedy